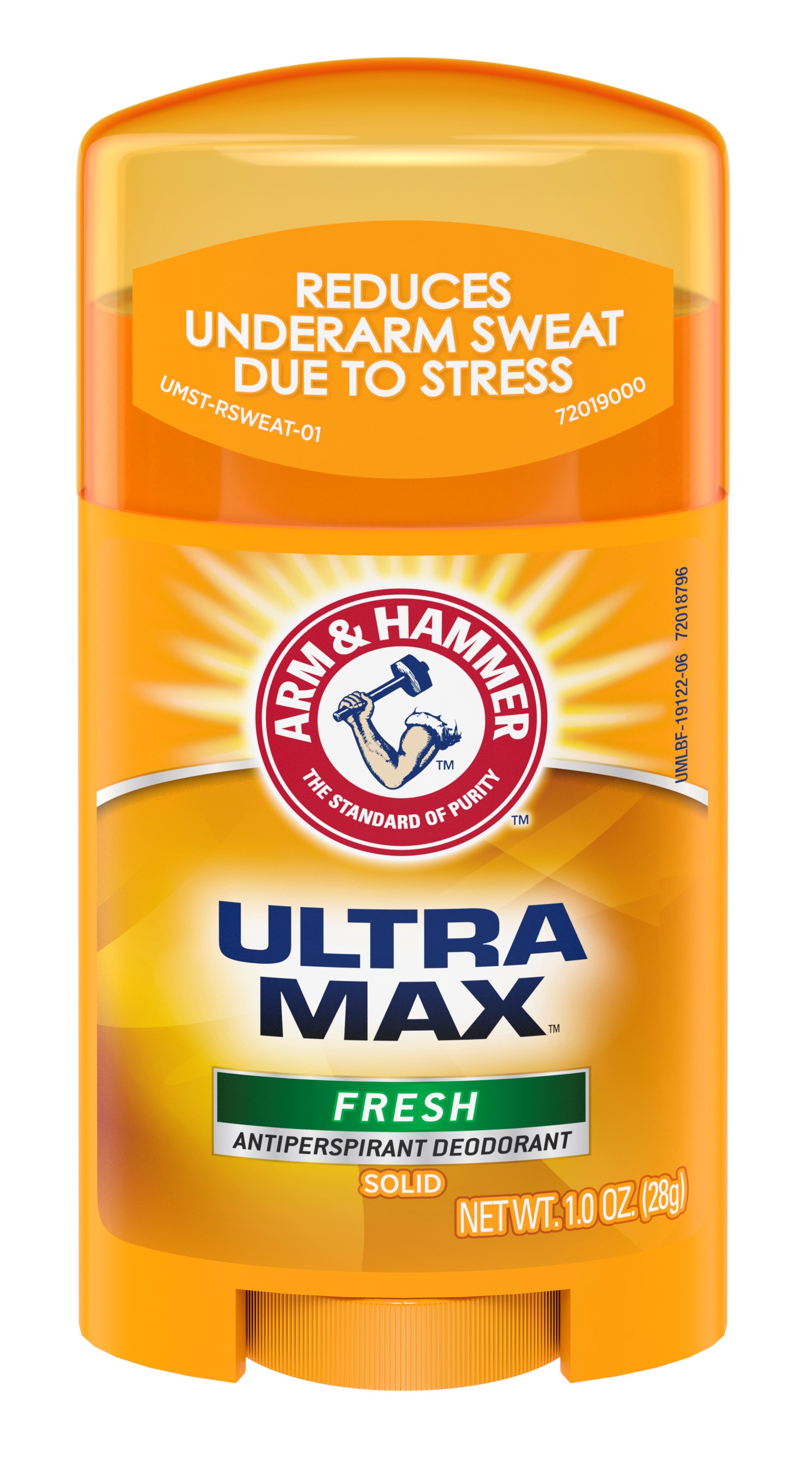 DRUG LABEL: UltraMax Invisible Solid - Fresh
NDC: 10237-869 | Form: STICK
Manufacturer: Church & Dwight Co., Inc.
Category: otc | Type: HUMAN OTC DRUG LABEL
Date: 20251204

ACTIVE INGREDIENTS: ALUMINUM CHLOROHYDRATE 0.19 g/1 g
INACTIVE INGREDIENTS: CYCLOMETHICONE 5; PPG-14 BUTYL ETHER; STEARYL ALCOHOL; HYDROGENATED CASTOR OIL; TALC; PETROLATUM; SODIUM BICARBONATE; C12-20 ALKYL BENZOATE; STARCH, CORN; XANTHAN GUM; MALTODEXTRIN

Arm and Hammer UltraMax Invisible Solid - Fresh Scent

ACTIVE INGREDIENT

Aluminum Chlorohydrate 19%

PURPOSE

Antiperspirant

Use

Usereduces underarm perspiration

WARNINGS

For external use only

Do not use onbroken skin

Stop use ifrash or irritation occurs

Ask a doctor before use if you havekidney disease

Keep out of reach of children.

If swallowed, get medical help or contact a Poison Control Center right away.

DOSAGE AND ADMINISTRATION

DirectionsApply a thin layer to underarms only

INACTIVE INGREDIENT

PPG-14 Butyl Ether, Cyclopentasiloxane, Stearyl Alcohol, C12-15 Alkyl Benzoate, Talc, Hydrogenated Castor Oil, Petrolatum, Fragance, Sodium Bicarbonate (Baking Soda), Corn Starch Modified, Polysaccharides, Maltodextrin

QUESTIONS

? Questions 1-800-248-8820M-F 9am-5pm ET

Principal Display

REDUCES

UNDERARM SWEAT

DUE TO STRESS

Arm and Hammer
The Standard of Purity

ULTRA MAX

FRESH
Antiperspirant Deodorant
SOLID

NET WT. 1.0 OZ. (28g)